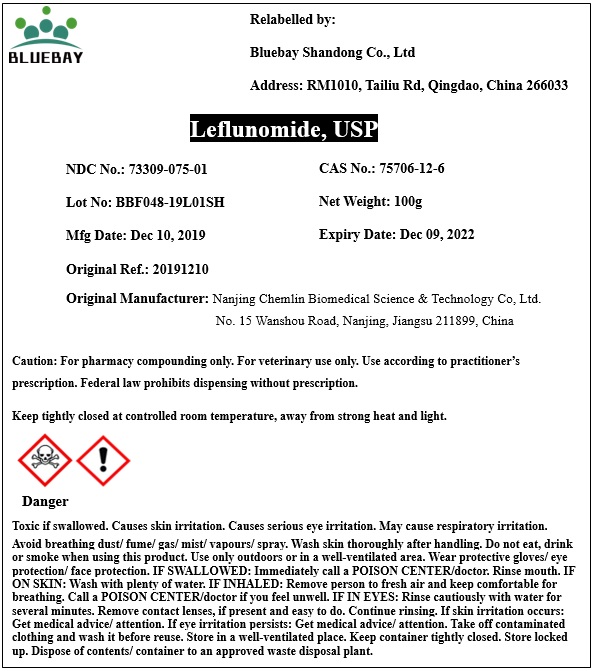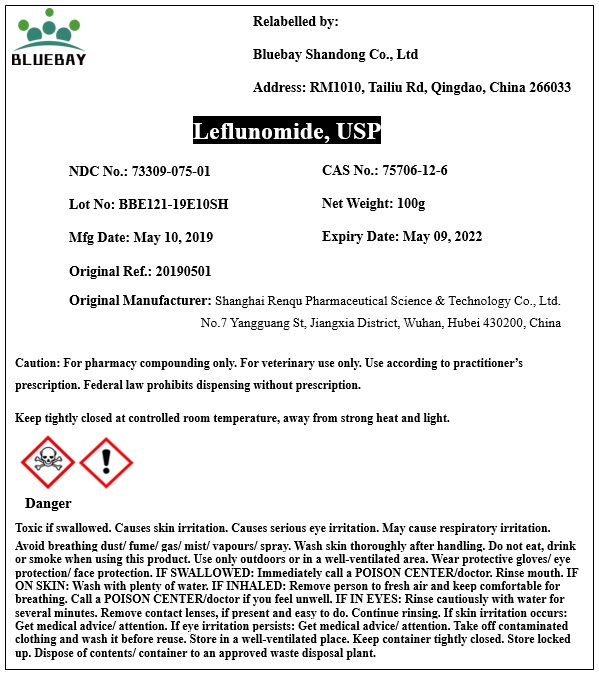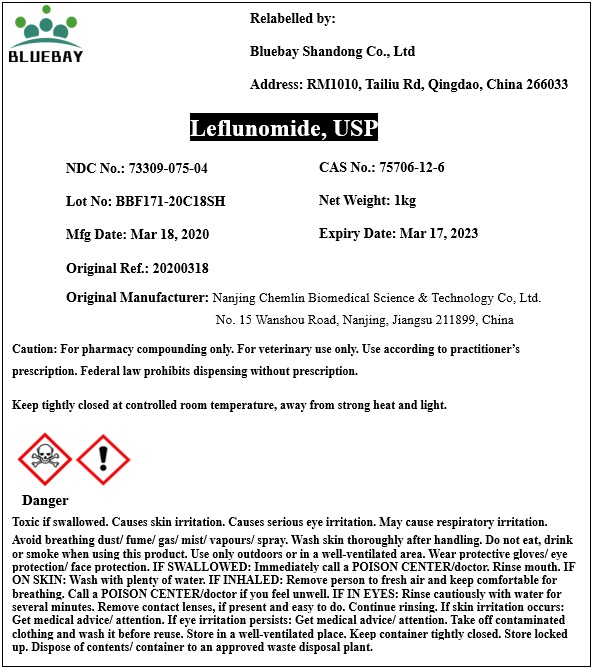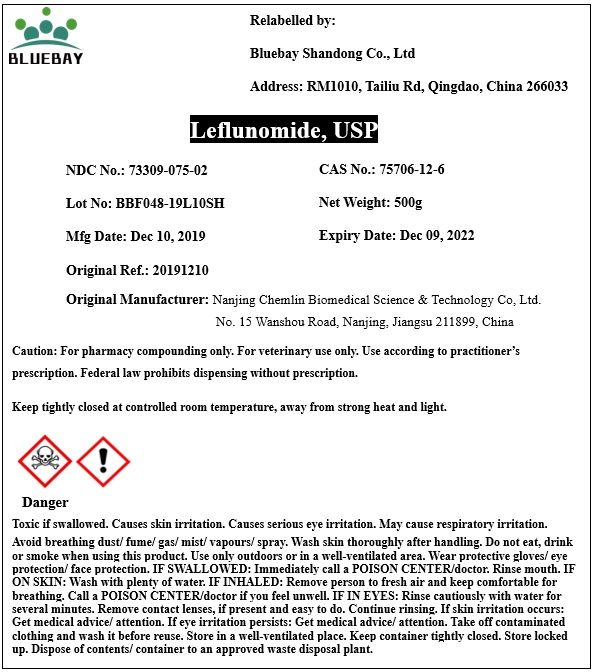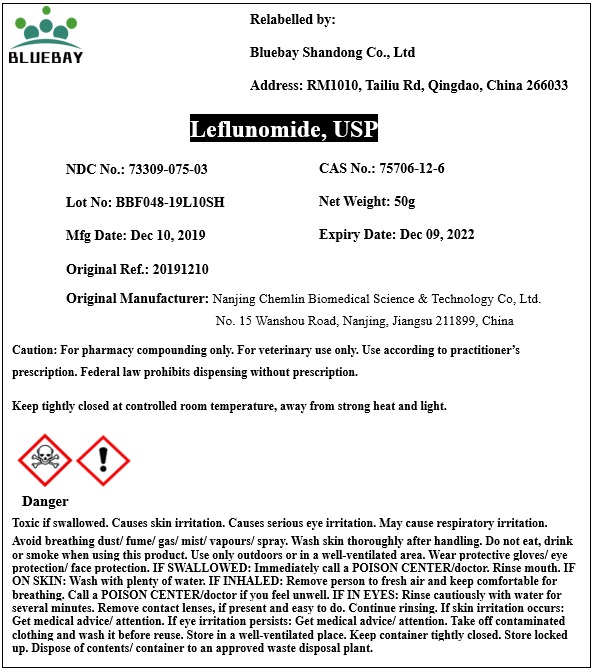 DRUG LABEL: Leflunomide
NDC: 73309-075 | Form: POWDER
Manufacturer: BLUEBAY SHANDONG CO.,LTD
Category: other | Type: BULK INGREDIENT
Date: 20200414

ACTIVE INGREDIENTS: Leflunomide 1 g/1 g

Leflunomide